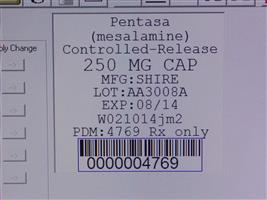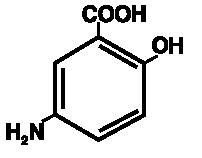 DRUG LABEL: Pentasa
NDC: 68151-4769 | Form: CAPSULE
Manufacturer: Carilion Materials Management
Category: prescription | Type: HUMAN PRESCRIPTION DRUG LABEL
Date: 20160806

ACTIVE INGREDIENTS: MESALAMINE 250 mg/1 1
INACTIVE INGREDIENTS: CASTOR OIL; SILICON DIOXIDE; STEARIC ACID; TALC; D&C YELLOW NO. 10; FD&C BLUE NO. 1; FD&C GREEN NO. 3; GELATIN; TITANIUM DIOXIDE

PENTASA®
(mesalamine)
Controlled-Release Capsules 250 mg and 500 mg
Prescribing Information as of 10/2015
Rx only

DESCRIPTION

PENTASA (mesalamine) for oral administration is a controlled-release formulation of mesalamine, an aminosalicylate anti-inflammatory agent for gastrointestinal use.

Chemically, mesalamine is 5-amino-2-hydroxybenzoic acid. It has a molecular weight of 153.14.

The structural formula is:

Each 250 mg capsule contains 250 mg of mesalamine. It also contains the following inactive ingredients: acetylated monoglyceride, castor oil, colloidal silicon dioxide, ethylcellulose, hydroxypropyl methylcellulose, starch, stearic acid, sugar, talc, and white wax. The capsule shell contains D&C Yellow #10, FD&C Blue #1, FD&C Green #3, gelatin, titanium dioxide, and other ingredients.

Each 500 mg capsule contains 500 mg of mesalamine. It also contains the following inactive ingredients: acetylated monoglyceride, castor oil, colloidal silicon dioxide, ethylcellulose, hydroxypropyl methylcellulose, starch, stearic acid, sugar, talc, and white wax. The capsule shell contains FD&C Blue #1, gelatin, titanium dioxide, and other ingredients.

CLINICAL PHARMACOLOGY

Sulfasalazine is split by bacterial action in the colon into sulfapyridine (SP) and mesalamine (5-ASA). It is thought that the mesalamine component is therapeutically active in ulcerative colitis. The usual oral dose of sulfasalazine for active ulcerative colitis in adults is 2 to 4 g per day in divided doses. Four grams of sulfasalazine provide 1.6 g of free mesalamine to the colon.

The mechanism of action of mesalamine (and sulfasalazine) is unknown, but appears to be topical rather than systemic. Mucosal production of arachidonic acid (AA) metabolites, both through the cyclooxygenase pathways, ie, prostanoids, and through the lipoxygenase pathways, ie, leukotrienes (LTs) and hydroxyeicosatetraenoic acids (HETEs), is increased in patients with chronic inflammatory bowel disease, and it is possible that mesalamine diminishes inflammation by blocking cyclooxygenase and inhibiting prostaglandin (PG) production in the colon.

Human Pharmacokinetics and Metabolism
Absorption. PENTASA is an ethylcellulose-coated, controlled-release formulation of mesalamine designed to release therapeutic quantities of mesalamine throughout the gastrointestinal tract. Based on urinary excretion data, 20% to 30% of the mesalamine in PENTASA is absorbed. In contrast, when mesalamine is administered orally as an unformulated 1-g aqueous suspension, mesalamine is approximately 80% absorbed.

Plasma mesalamine concentration peaked at approximately 1 μg/mL 3 hours following a 1-g PENTASA dose and declined in a biphasic manner. The literature describes a mean terminal half-life of 42 minutes for mesalamine following intravenous administration. Because of the continuous release and absorption of mesalamine from PENTASA throughout the gastrointestinal tract, the true elimination half-life cannot be determined after oral administration. N-acetylmesalamine, the major metabolite of mesalamine, peaked at approximately 3 hours at 1.8 μg/mL, and its concentration followed a biphasic decline. Pharmacological activities of N-acetylmesalamine are unknown, and other metabolites have not been identified.

Oral mesalamine pharmacokinetics were nonlinear when PENTASA capsules were dosed from 250 mg to 1 g four times daily, with steady-state mesalamine plasma concentrations increasing about nine times, from 0.14 μg/mL to 1.21 μg/mL, suggesting saturable first-pass metabolism. N-acetylmesalamine pharmacokinetics were linear.

Elimination. About 130 mg free mesalamine was recovered in the feces following a single 1-g PENTASA dose, which was comparable to the 140 mg of mesalamine recovered from the molar equivalent sulfasalazine tablet dose of 2.5 g. Elimination of free mesalamine and salicylates in feces increased proportionately with PENTASA dose. N-acetylmesalamine was the primary compound excreted in the urine (19% to 30%) following PENTASA dosing.

CLINICAL TRIALS

In two randomized, double-blind, placebo-controlled, dose-response trials (UC-1 and UC-2) of 625 patients with active mild to moderate ulcerative colitis, PENTASA, at an oral dose of 4 g/day given 1 g four times daily, produced consistent improvement in prospectively identified primary efficacy parameters, PGA, Tx F, and SI as shown in the table below.

The 4-g dose of PENTASA also gave consistent improvement in secondary efficacy parameters, namely the frequency of trips to the toilet, stool consistency, rectal bleeding, abdominal/rectal pain, and urgency. The 4-g dose of PENTASA induced remission as assessed by endoscopic and symptomatic endpoints.

In some patients, the 2-g dose of PENTASA was observed to improve efficacy parameters measured. However, the 2-g dose gave inconsistent results in primary efficacy parameters across the two adequate and well-controlled trials.

Parameter Evaluated | Clinical Trial UC-1 |  |  | Clinical Trial-UC-2
Parameter Evaluated | PL (n=90) | PENTASA |  | PL (n=83) | PENTASA
Parameter Evaluated | PL (n=90) | 4 g/day (n=95) | 2 g/day (n=97) | PL (n=83) | 4 g/day (n=85) | 2 g/day (n=83)
PGA | 36% | 59%* | 57%* | 31% | 55%* | 41%
Tx F | 22% | 9%* | 18% | 31% | 9%* | 17%*
SI | -2.5 | -5.0* | -4.3* | -1.6 | -3.8* | -2.6
Remission^+ | 12% | 26%* | 24%* | 12% | 27%* | 12%
* p<0.05 vs placebo.
PGA: Physician Global Assessment: proportion of patients with complete or marked improvement.
Tx F: Treatment Failure: proportion of patients developing severe or fulminant UC requiring steroid therapy or hospitalization or worsening of the disease at 7 days of therapy, or lack of significant improvement by 14 days of therapy.
SI: Sigmoidoscopic Index: an objective measure of disease activity rated by a standard (15-point) scale that includes mucosal vascular pattern, erythema, friability, granularity/ulcerations, and mucopus: improvement over baseline.
^+ Defined as complete resolution of symptoms plus improvement of endoscopic endpoints. To be considered in remission, patients had a "1" score for one of the endoscopic components (mucosal vascular pattern, erythema, granularity, or friability) and "0" for the others.

INDICATIONS AND USAGE

PENTASA is indicated for the induction of remission and for the treatment of patients with mildly to moderately active ulcerative colitis.

CONTRAINDICATIONS

PENTASA is contraindicated in patients who have demonstrated hypersensitivity to mesalamine, any other components of this medication, or salicylates.

PRECAUTIONS

General

Caution should be exercised if PENTASA is administered to patients with impaired hepatic function.

Mesalamine has been associated with an acute intolerance syndrome that may be difficult to distinguish from a flare of inflammatory bowel disease. Although the exact frequency of occurrence cannot be ascertained, it has occurred in 3% of patients in controlled clinical trials of mesalamine or sulfasalazine. Symptoms include cramping, acute abdominal pain and bloody diarrhea, sometimes fever, headache, and rash. If acute intolerance syndrome is suspected, prompt withdrawal is required. If a rechallenge is performed later in order to validate the hypersensitivity, it should be carried out under close medical supervision at reduced dose and only if clearly needed.

Renal

Caution should be exercised if PENTASA is administered to patients with impaired renal function. Single reports of nephrotic syndrome and interstitial nephritis associated with mesalamine therapy have been described in the foreign literature. There have been rare reports of interstitial nephritis in patients receiving PENTASA. In animal studies, a 13-week oral toxicity study in mice and 13-week and 52-week oral toxicity studies in rats and cynomolgus monkeys have shown the kidney to be the major target organ of mesalamine toxicity. Oral daily doses of 2400 mg/kg in mice and 1150 mg/kg in rats produced renal lesions including granular and hyaline casts, tubular degeneration, tubular dilation, renal infarct, papillary necrosis, tubular necrosis, and interstitial nephritis. In cynomolgus monkeys, oral daily doses of 250 mg/kg or higher produced nephrosis, papillary edema, and interstitial fibrosis. Patients with preexisting renal disease, increased BUN or serum creatinine, or proteinuria should be carefully monitored, especially during the initial phase of treatment. Mesalamine-induced nephrotoxicity should be suspected in patients developing renal dysfunction during treatment.

Interference with Laboratory Tests

Use of mesalamine may lead to spuriously elevated test results when measuring urinary normetanephrine by liquid chromatography with electrochemical detection, because of the similarity in the chromatograms of normetanephrine and mesalamine's main metabolite, N-acetylaminosalicylic acid (N-Ac-5-ASA). An alternative, selective assay for normetanephrine should be considered.

Drug Interactions

There are no data on interactions between PENTASA and other drugs.

Carcinogenesis, Mutagenesis, Impairment of Fertility

In a 104-week dietary carcinogenicity study of mesalamine, CD-1 mice were treated with doses up to 2500 mg/kg/day and it was not tumorigenic. For a 50 kg person of average height (1.46 m^2 body surface area), this represents 2.5 times the recommended human dose on a body surface area basis (2960 mg/m^2/day). In a 104-week dietary carcinogenicity study in Wistar rats, mesalamine up to a dose of 800 mg/kg/day was not tumorigenic. This dose represents 1.5 times the recommended human dose on a body surface area basis.

No evidence of mutagenicity was observed in an in vitro Ames test and in an in vivo mouse micronucleus test.

No effects on fertility or reproductive performance were observed in male or female rats at oral doses of mesalamine up to 400 mg/kg/day (0.8 times the recommended human dose based on body surface area).

Semen abnormalities and infertility in men, which have been reported in association with sulfasalazine, have not been seen with PENTASA capsules during controlled clinical trials.

Pregnancy

Category B. Reproduction studies have been performed in rats at doses up to 1000 mg/kg/day (5900 mg/M^2) and rabbits at doses of 800 mg/kg/day (6856 mg/M^2) and have revealed no evidence of teratogenic effects or harm to the fetus due to mesalamine. There are, however, no adequate and well-controlled studies in pregnant women. Because animal reproduction studies are not always predictive of human response, PENTASA should be used during pregnancy only if clearly needed.

Mesalamine is known to cross the placental barrier.

Nursing Mothers

Minute quantities of mesalamine were distributed to breast milk and amniotic fluid of pregnant women following sulfasalazine therapy. When treated with sulfasalazine at a dose equivalent to 1.25 g/day of mesalamine, 0.02 μg/mL to 0.08 μg/mL and trace amounts of mesalamine were measured in amniotic fluid and breast milk, respectively. N-acetylmesalamine, in quantities of 0.07 μg/mL to 0.77 μg/mL and 1.13 μg/mL to 3.44 μg/mL, was identified in the same fluids, respectively.

Caution should be exercised when PENTASA is administered to a nursing woman.

No controlled studies with PENTASA during breast-feeding have been carried out. Hypersensitivity reactions like diarrhea in the infant cannot be excluded.

Pediatric Use

Safety and efficacy of PENTASA in pediatric patients have not been established.

ADVERSE REACTIONS

In combined domestic and foreign clinical trials, more than 2100 patients with ulcerative colitis or Crohn's disease received PENTASA therapy. Generally, PENTASA therapy was well tolerated. The most common events (ie, greater than or equal to 1%) were diarrhea (3.4%), headache (2.0%), nausea (1.8%), abdominal pain (1.7%), dyspepsia (1.6%), vomiting (1.5%), and rash (1.0%).

In two domestic placebo-controlled trials involving over 600 ulcerative colitis patients, adverse events were fewer in PENTASA® (mesalamine)-treated patients than in the placebo group (PENTASA 14% vs placebo 18%) and were not dose-related. Events occurring in more than 1% are shown in the table below. Of these, only nausea and vomiting were more frequent in the PENTASA group. Withdrawal from therapy due to adverse events was more common on placebo than PENTASA (7% vs 4%).

Table 1. Adverse Events Occurring in More than 1% of Either Placebo or PENTASA Patients in Domestic Placebo-controlled Ulcerative Colitis Trials. (PENTASA Comparison to Placebo)
Event | PENTASA n=451 | Placebo n=173
Diarrhea Headache Nausea Abdominal Pain Melena (Bloody Diarrhea) Rash Anorexia Fever Rectal Urgency Nausea and Vomiting Worsening of Ulcerative Colitis Acne | 16 (3.5%) 10 (2.2%) 14 (3.1%) 5 (1.1%) 4 (0.9%) 6 (1.3%) 5 (1.1%) 4 (0.9%) 1 (0.2%) 5 (1.1%) 2 (0.4%) 1 (0.2%) | 13 (7.5%) 6 (3.5%) ----- 7 (4.0%) 6 (3.5%) 2 (1.2%) 2 (1.2%) 2 (1.2%) 4 (2.3%) ----- 2 (1.2%) 2 (1.2%)

Clinical laboratory measurements showed no significant abnormal trends for any test, including measurement of hematological, liver, and kidney function.

The following adverse events, presented by body system, were reported infrequently (ie, less than 1%) during domestic ulcerative colitis and Crohn's disease trials. In many cases, the relationship to PENTASA has not been established.

Gastrointestinal: abdominal distention, anorexia, constipation, duodenal ulcer, dysphagia, eructation, esophageal ulcer, fecal incontinence, GGTP increase, GI bleeding, increased alkaline phosphatase, LDH increase, mouth ulcer, oral moniliasis, pancreatitis, rectal bleeding, SGOT increase, SGPT increase, stool abnormalities (color or texture change), thirst

Dermatological: acne, alopecia, dry skin, eczema, erythema nodosum, nail disorder, photosensitivity, pruritus, sweating, urticaria

Nervous System: depression, dizziness, insomnia, somnolence, paresthesia

Cardiovascular: palpitations, pericarditis, vasodilation

Other: albuminuria, amenorrhea, amylase increase, arthralgia, asthenia, breast pain, conjunctivitis, ecchymosis, edema, fever, hematuria, hypomenorrhea, Kawasaki-like syndrome, leg cramps, lichen planus, lipase increase, malaise, menorrhagia, metrorrhagia, myalgia, pulmonary infiltrates, thrombocythemia, thrombocytopenia, urinary frequency

One week after completion of an 8-week ulcerative colitis study, a 72-year-old male, with no previous history of pulmonary problems, developed dyspnea. The patient was subsequently diagnosed with interstitial pulmonary fibrosis without eosinophilia by one physician and bronchiolitis obliterans with organizing pneumonitis by a second physician. A causal relationship between this event and mesalamine therapy has not been established.

Published case reports and/or spontaneous postmarketing surveillance have described infrequent instances of pericarditis, fatal myocarditis, chest pain and T-wave abnormalities, hypersensitivity pneumonitis, pancreatitis, nephrotic syndrome, interstitial nephritis, hepatitis, aplastic anemia, pancytopenia, leukopenia, agranulocytosis, or anemia while receiving mesalamine therapy. Anemia can be a part of the clinical presentation of inflammatory bowel disease. Allergic reactions, which could involve eosinophilia, can be seen in connection with PENTASA therapy.

Postmarketing Reports
The following events have been identified during post-approval use of the PENTASA brand of mesalamine in clinical practice. Because they are reported voluntarily from a population of unknown size, estimates of frequency cannot be made. These events have been chosen for inclusion due to a combination of seriousness, frequency of reporting, or potential causal connection to mesalamine:

Gastrointestinal: Reports of hepatotoxicity, including elevated liver enzymes (SGOT/AST, SGPT/ALT, GGT, LDH, alkaline phosphatase, bilirubin), hepatitis, jaundice, cholestatic jaundice, cirrhosis, and possible hepatocellular damage including liver necrosis and liver failure. Some of these cases were fatal. One case of Kawasaki-like syndrome which included hepatic function changes was also reported.

Other: Postmarketing reports of anaphylactic reaction, Steven-Johnson syndrome (SJS), drug reaction with eosinophilia and systemic symptoms (DRESS), pneumonitis, granulocytopenia, systemic lupus erythematosis, acute renal failure, chronic renal failure and angioedema have been received in patients taking PENTASA.

OVERDOSAGE

Single oral doses of mesalamine up to 5 g/kg in pigs or a single intravenous dose of mesalamine at 920 mg/kg in rats were not lethal.

There is no clinical experience with PENTASA overdosage. PENTASA is an aminosalicylate, and symptoms of salicylate toxicity may be possible, such as: tinnitus, vertigo, headache, confusion, drowsiness, sweating, hyperventilation, vomiting, and diarrhea. Severe intoxication with salicylates can lead to disruption of electrolyte balance and blood-pH, hyperthermia, and dehydration.

Treatment of Overdosage. Since PENTASA is an aminosalicylate, conventional therapy for salicylate toxicity may be beneficial in the event of acute overdosage. This includes prevention of further gastrointestinal tract absorption by emesis and, if necessary, by gastric lavage. Fluid and electrolyte imbalance should be corrected by the administration of appropriate intravenous therapy. Adequate renal function should be maintained.

DOSAGE AND ADMINISTRATION

The recommended dosage for the induction of remission and the symptomatic treatment of mildly to moderately active ulcerative colitis is 1g (4 PENTASA 250 mg capsules or 2 PENTASA 500 mg capsules) 4 times a day for a total daily dosage of 4g. Treatment duration in controlled trials was up to 8 weeks.

PENTASA capsules may be swallowed whole, or alternatively, the capsule may be opened and the entire contents sprinkled onto applesauce or yogurt. The entire contents should be consumed immediately. The capsules and capsule contents must not be crushed or chewed.

Safety and efficacy of PENTASA in pediatric patients have not been established.

HOW SUPPLIED

Product: 68151-4769

NDC: 68151-4769-8 1 CAPSULE in a PACKAGE